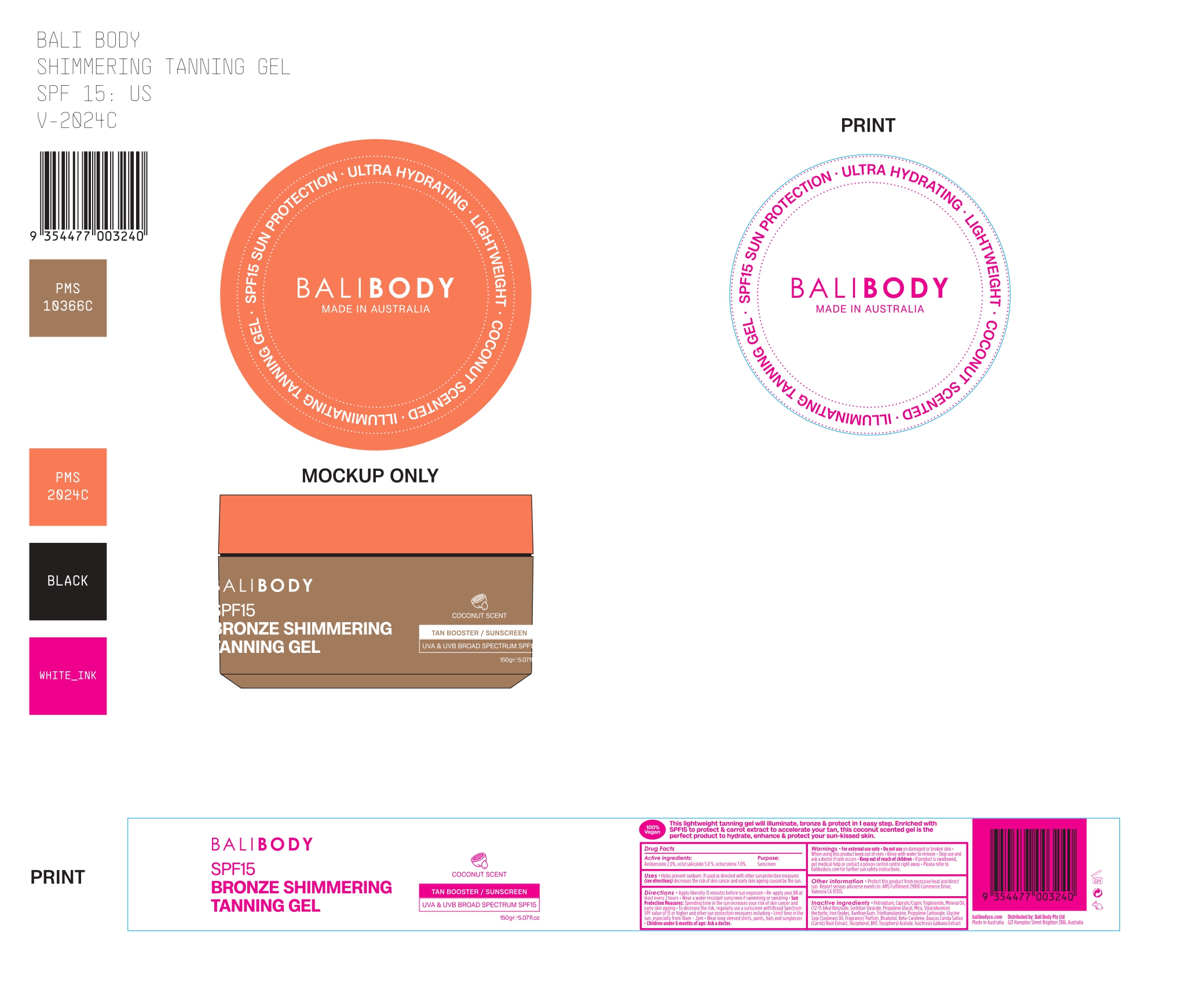 DRUG LABEL: BaliBody SPF15 Bronze Shimmering Tanning Gel
NDC: 70157-024 | Form: GEL
Manufacturer: Baxter Laboratories Pty. Ltd.
Category: otc | Type: HUMAN OTC DRUG LABEL
Date: 20241203

ACTIVE INGREDIENTS: OCTOCRYLENE 7 g/100 g; AVOBENZONE 2 g/100 g; OCTISALATE 5 g/100 g
INACTIVE INGREDIENTS: IRON OXIDES; MICA; ISOCHRYSIS GALBANA WHOLE; STEARALKONIUM HECTORITE; MINERAL OIL; TRIETHANOLAMINE; BETA-CAROTENE; BHT; BISABOLOL; SORBITAN STEARATE; PROPYLENE GLYCOL; XANTHAN GUM; TOCOPHEROL; .ALPHA.-TOCOPHEROL ACETATE; PETROLATUM; C12-15 ALKYL BENZOATE; PROPYLENE CARBONATE; GLYCINE SOJA (SOYBEAN) OIL; CARROT; CAPRYLIC/CAPRIC TRIGLYCERIDE

BaliBody SPF15 Bronze Shimmering Tanning Gel

Active Ingredients: Purpose:

Avobenzone 2.0%, Octyl Salicylate 5.0%, Octocrylene 7.0% Sunscreen

Uses

Helps prevent sunburn. If used as directed with other sun protection measures (see directions) decreases the risk of skin cancer and early skin ageing caused by the sun.

Keep out of reach of children.

Stop use and ask a doctor if rash occurs.

Warnings

For external use only. Do not use on damaged or broken skin. When using this product keep ou tof eyes. Rinse with water to remove. If product is swallowed, get medical help or contact a poison control center right away. Please refer to balibodyco.com for further sun safety instructions.

Directions

Apply liberally 15 minutes before sun exposure. Re-apply your BB at least every 2 hours. Wear a water resistant sunscreen if swimming or sweating. Sun Protection Measures: Spending time in the sun increases your risk of skin cancer and early skin ageing. To decrease the risk, regularly use a sunscreen with Broad Spectrum SPF value of 15 or higher and other sun protective measures including. Limit time in the sun, especially from 10am-2pm. Wear long sleeved shirts, parts, hats and sunglasses. Children under 6 months of age: Ask a doctor.

INACTIVE INGREDIENT

Inactive ingredients: Petrolatum, Caprylic/Capric Triglyceride, Mineral Oil, C12-15 Alkyl Benzoate, Sorbitan Stearate, Propylene Glycol, Mica, Stearalkonium Hectorite, Iron Oxides, Xanthan Gum, Triethanolamine, Propylene Carbonate, Glycine Soja (Soybean) Oil, Fragrance/Parfum, Bisabolol, Beta-Carolene, Daucus Carota Sativa (Carrot) Root Extract, Tocopherol, BHT, Tocopheryl Acetate, Isochrysis Galbana Extract.

Other information: Protect this product from excessive heat and direct sun. Report serious adverse events to: AMS Fullfilment 29010 Commerce Drive, Valencia CA 91355.

PACKAGE LABEL

BaliBody

SPF 15 Bronze Shimmering Tanning Gel

150g 5.07fl.oz